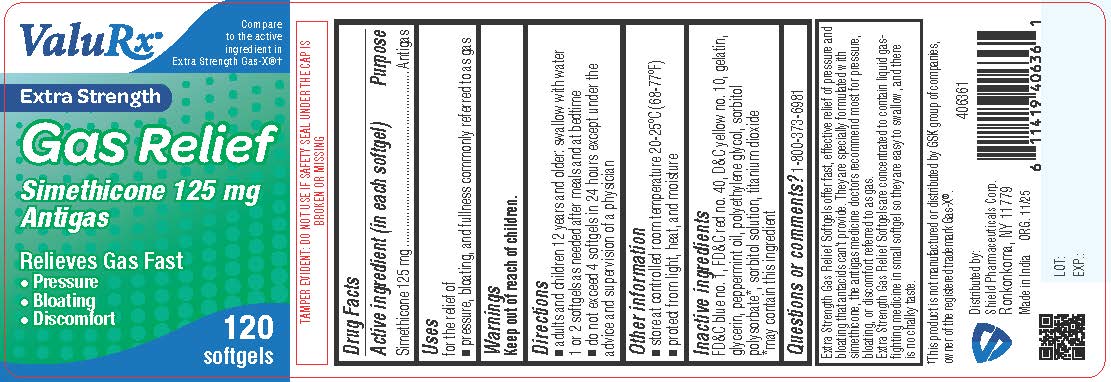 DRUG LABEL: Extra Strength Gas Relief
NDC: 83059-0118 | Form: CAPSULE, LIQUID FILLED
Manufacturer: Shield Pharmaceuticals Corp
Category: otc | Type: HUMAN OTC DRUG LABEL
Date: 20260224

ACTIVE INGREDIENTS: DIMETHICONE 125 mg/1 1
INACTIVE INGREDIENTS: FD&C BLUE NO. 1; FD&C RED NO. 40; D&C YELLOW NO. 10; GELATIN; GLYCERIN; SORBITOL; PEPPERMINT OIL; POLYETHYLENE GLYCOL 400; POVIDONE; PROPYLENE GLYCOL; TITANIUM DIOXIDE

Extra Strength Gas Relief

Drug Facts

Active ingredient (in each softgel)

Simethicone 125 mg

Purpose

Antigas

Uses

for the relief of

- pressure, bloating, and fullness commonly referred to as gas

Warnings

Keep out of reach of children.

Directions

- adults and children 12 years and older: swallow with water 1 or 2 softgels as needed after meals and at bedtime
- do not exceed 4 softgels in 24 hours except under the advice and supervision of a physician

Other information

- store at controlled room temperature 20-25ºC (68-77ºF)
- protect from light, heat, and moisture

Inactive ingredients

FD & C blue #01*, FD&C red #40, FD&C yellow #6*, FD&C yellow #10, gelatin, glycerin, peppermint oil, polyethylene glycol*, povidone*, propylene glycol*, sorbitol solution, titanium dioxide *may contain this inactive ingredient

Questions or comments?

1-800-373-6981

Additional information

Extra Strength Gas ReliefSoftgels offer fast, effective relief of pressure and bloating that antacids can’t provide. They are specially formulated with simethicone, the antigas medicine doctors recommend most for pressure, bloating, or discomfort referred to as gas.

Extra Strength Gas ReliefSoftgels are concentrated to contain liquid gas-fighting medicine in a small softgels so they are easy to swallow, and there is no chalky taste.

TAMPER EVIDENT: DO NOT USE IF CARTON IS OPENED OR SAFETY SEAL UNDER CAP IS BROKEN OR MISSING.
KEEP OUTER CARTON FOR COMPLETE WARNINGS AND PRODUCT INFORMATION.

Distributed by:
Shield Pharmaceuticals Corp.
Ronkonkoma, NY 11779

PRINCIPAL DISPLAY PANEL

ValuRx

Extra StrengthGas Relief

Simethicone 125 mg
Antigas

Relieves Gas Fast

- Pressure
- Bloating
- Discomfort